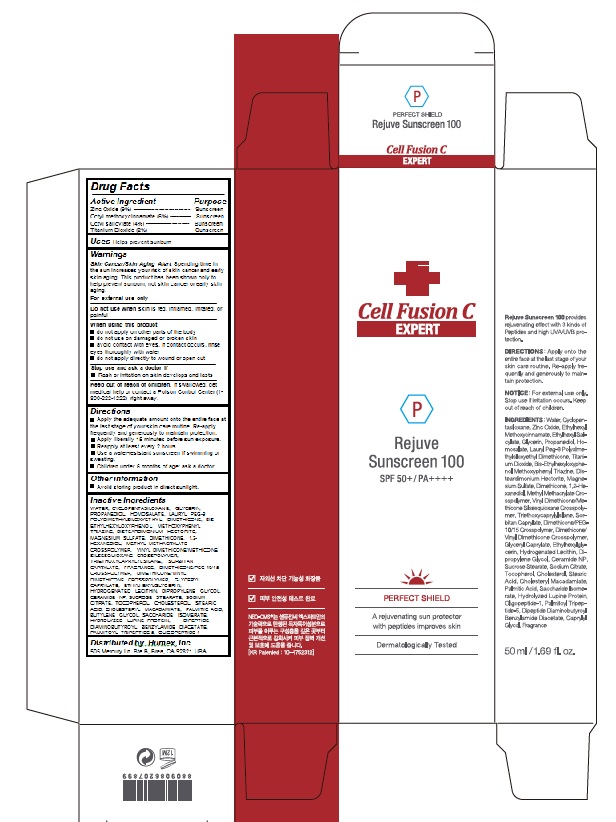 DRUG LABEL: Perfect Shield Rejuve Sunscreen 100
NDC: 52554-1116 | Form: CREAM
Manufacturer: CMS LAB Inc
Category: otc | Type: HUMAN OTC DRUG LABEL
Date: 20180530

ACTIVE INGREDIENTS: ZINC OXIDE 4.5 g/50 mL; OCTISALATE 2 g/50 mL; TITANIUM DIOXIDE 1 g/50 mL; OCTINOXATE 3 g/50 mL
INACTIVE INGREDIENTS: WATER 21.14 g/50 mL

Perfect Shield Rejuve Sunscreen 100

Active Ingredient

Zinc Oxide (9%) ------------------------------- Sunscreen
Octinoxate (6%) ------------------------------- Sunscreen
Octisalate (4%) -------------------------------- Sunscreen
Titanium Dioxide (2%) ----------------------- Sunscreen

Purpose

Sunscreen

Warnings

Skin Cancer/Skin Aging Alert: Spending time in the sun increases your risk of skin cancer and early skin aging. This product has been shown only to help prevent sunburn, not skin cancer or early skin aging.

For external use only

Do not use when

skin is red, inflamed, irritated, or painful

Directions

Apply the adequate amount onto the entire face at the last stage of your skin care routine. Re-apply frequently and generously to maintain protection.

Apply liberally 15 minutes before sun exposure.

Reapply at least every 2 hours.

Use a water-resistant sunscreen if swimming or sweating.

Children under 6 months of age: ask a doctor

Keep out of reach of children

If swallowed, get medical help or contact a Poison Control Center (1-800-222-1222) right away.

Uses

Helps prevent sunburn

Inactive Ingredients

WATER, CYCLOPENTASILOXANE, GLYCERIN, PROPANEDIOL, HOMOSALATE, LAURYL PEG-9 POLYDIMETHYLSILOXYETHYL DIMETHICONE, BIS-ETHYLHEXYLOXYPHENOL METHOXYPHENYL TRIAZINE, DISTEARDIMONIUM HECTORITE, MAGNESIUM SULFATE, DIMETHICONE, 1,2-HEXANEDIOL, METHYL METHACRYLATE CROSSPOLYMER, VINYL DIMETHICONE/METHICONE SILSESQUIOXANE CROSSPOLYMER, TRIETHOXYCAPRYLYLSILANE, SORBITAN CAPRYLATE, FRAGRANCE, DIMETHICONE/PEG-10/15 CROSSPOLYMER, DIMETHICONE/VINYL DIMETHICONE CROSSPOLYMER, GLYCERYL CAPRYLATE, ETHYLHEXYLGLYCERIN, HYDROGENATED LECITHIN, DIPROPYLENE GLYCOL, CERAMIDE NP, SUCROSE STEARATE, SODIUM CITRATE, TOCOPHEROL, CHOLESTEROL, STEARIC ACID, CHOLESTERYL MACADAMIATE, PALMITIC ACID, BUTYLENE GLYCOL, SACCHARIDE ISOMERATE, HYDROLYZED LUPINE PROTEIN, DIPEPTIDE DIAMINOBUTYROYL BENZYLAMIDE DIACETATE, PALMITOYL TRIPEPTIDE-5, OLIGOPEPTIDE-1